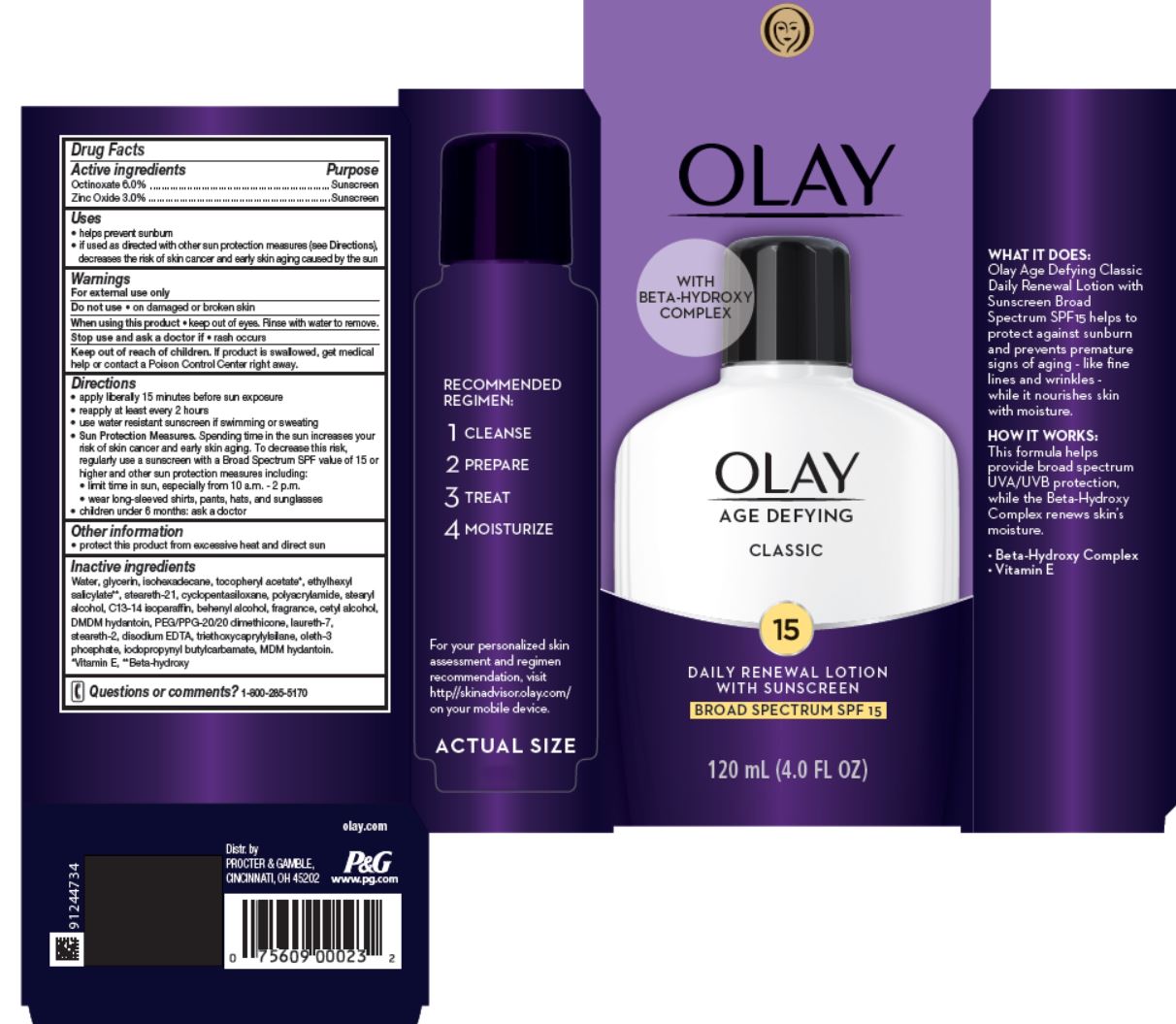 DRUG LABEL: Olay Age Defying Classic Daily Renewal
NDC: 69423-259 | Form: LOTION
Manufacturer: The Procter & Gamble Manufacturing Company
Category: otc | Type: HUMAN OTC DRUG LABEL
Date: 20251231

ACTIVE INGREDIENTS: OCTINOXATE 6 g/100 mL; ZINC OXIDE 3 g/100 mL
INACTIVE INGREDIENTS: WATER; GLYCERIN; ISOHEXADECANE; .ALPHA.-TOCOPHEROL ACETATE; STEARETH-21; CYCLOMETHICONE 5; STEARYL ALCOHOL; DOCOSANOL; C13-14 ISOPARAFFIN; OCTISALATE; CETYL ALCOHOL; DMDM HYDANTOIN; PEG/PPG-20/20 DIMETHICONE; STEARETH-2; EDETATE DISODIUM; LAURETH-7; TRIETHOXYCAPRYLYLSILANE; OLETH-3 PHOSPHATE; IODOPROPYNYL BUTYLCARBAMATE; POLYACRYLAMIDE (1300000 MW)

Olay® Age Defying Classic Daily Renewal
Broad Spectrum SPF 15

Drug Facts

ACTIVE INGREDIENT

Active ingredients | Purpose
Octinoxate 6.0% | Sunscreen
Zinc Oxide 3.0% | Sunscreen

Uses

- helps prevent sunburn
- if used as directed with other sun protection measures (see Directions), decreases the risk of skin cancer and early skin aging caused by the sun

Warnings

For external use only

Do not use on damaged or broken skin

When using this product keep out of eyes. Rinse with water to remove.

Stop use and ask a doctor if rash occurs

Keep out of reach of children. If product is swallowed, get medical help or contact a Poison Control Center right away.

Directions

- apply liberally 15 minutes before sun exposure
- reapply at least every 2 hours
- use water resistant sunscreen if swimming or sweating
- Sun Protection Measures. Spending time in the sun increases your risk of skin cancer and early skin aging. To decrease this risk, regularly use a sunscreen with a Broad Spectrum SPF value of 15 or higher and other sun protection measures including:
  - limit time in sun, especially from 10 a.m. – 2 p.m.
  - wear long-sleeved shirts, pants, hats, and sunglasses
- children under 6 months: ask a doctor

Other information

- protect this product from excessive heat and direct sun

Inactive ingredients

Water, glycerin, isohexadecane, tocopheryl acetate*, ethylhexyl salicylate**, steareth-21, cyclopentasiloxane, polyacrylamide, stearyl alcohol, C13-14 isoparaffin, behenyl alcohol, fragrance, cetyl alcohol, DMDM hydantoin, PEG/PPG-20/20 dimethicone, laureth-7, steareth-2, disodium EDTA, triethoxycaprylylsilane, oleth-3 phosphate, iodopropynyl butylcarbamate, MDM hydantoin.
*Vitamin E, **Beta-hydroxy

Questions or comments?

Call 1-800-285-5170

Dist. by
PROCTER & GAMBLE, CINCINNATI, OH 45202

PRINCIPAL DISPLAY PANEL - 120 mL Bottle Carton

Olay®
AGE DEFYING

CLASSIC

15

DAILY RENEWAL LOTION
with sunscreen
BROAD SPECTRUM SPF 15

120 mL (4.0 FL OZ)